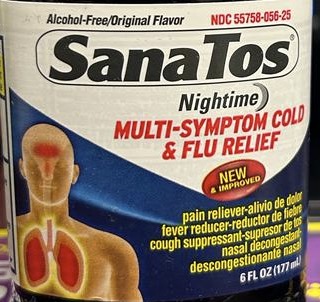 DRUG LABEL: Sanatos Nighttime Multi Symptoms
NDC: 55758-056 | Form: LIQUID
Manufacturer: Pharmadel LLC
Category: otc | Type: HUMAN OTC DRUG LABEL
Date: 20231122

ACTIVE INGREDIENTS: DOXYLAMINE SUCCINATE 12.5 mg/30 mL; DEXTROMETHORPHAN HYDROBROMIDE 30 mg/30 mL; ACETAMINOPHEN 650 mg/30 mL
INACTIVE INGREDIENTS: ANHYDROUS CITRIC ACID; FD&C GREEN NO. 3; D&C YELLOW NO. 10; SACCHARIN SODIUM; SODIUM BENZOATE; SODIUM CITRATE; PROPYLENE GLYCOL; SUCROSE; WATER; FD&C YELLOW NO. 6; GLYCERIN; POLYETHYLENE GLYCOL, UNSPECIFIED

Sanatos MS Nighttime 6 (APTA)

Active Ingredients & Purposes

PURPOSE

Active ingredients (in each 30 mL dose cup) | Purposes
Acetaminophen 650 mg..... | Pain reliever/ fever reducer
Dextromethorphan HBr 30 mg..... | Cough suppressant
Doxylamine succinate 12.5 mg..... | Antihistamine

Uses

temporarily relieves these common cold/flu symptoms:

- sore throat
- headache
- minor aches and pains
- fever

- runny nose and sneezing
- cough due to minor throat and bronchial irritation

Warnings

Liver warning: This product contains acetaminophen. Severe liver damage may occur if you take:

- more than 4,000 mg of acetaminophen in 24 hours
- with other drugs containing acetaminophen
- 3 or more alcoholic drinks everyday while using this product

Allergy Alert: Acetaminophen may cause severe skin reactions. Symptoms may include:

- skin reddening
- blisters
- rash

If a skin reaction occurs, stop use and seek medical help right away.

Sore throat warning: If sore throat is severe, persists for more than 2 days, is accompanied or followed by fever, headache, rash, nausea, or vomiting, consult a doctor promptly.

Do not use

- with any other drug containing acetaminophen (prescription or nonprescription). If you are not sure whether a drug contains acetaminophen, ask a doctor or pharmacist.
- if you are now taking a prescription monoamine oxidase inhibitor (MAOI) (certain drugs for depression, psychiatric or emotional conditions, or Parkinson's disease), or for 2 weeks after stopping the MAOI drug. If you do not know if your prescription drug contains an MAOI, ask a doctor or pharmacist before taking this product.
- to make a child sleepy

Ask a doctor before use if you have

- a sodium-restricted diet
- liver disease
- glaucoma
- cough that occurs with too much phlegm (mucus)
- a breathing problem or chronic cough that lasts or as occurs with smoking, asthma, chronic bronchitis, or emphysema
- trouble urinating due to enlarged prostate gland

Ask a doctor or pharmacist before use if you are

- taking sedatives or tranquilizers
- taking the blood thinning drug warfarin

When using this product

- do not use more than directed
- avoid alcoholic drinks
- excitability may occur, especially in children
- marked drowsiness may occur
- be careful when driving a motor vehicle or operating machinery
- alcohol, sedatives, and tranquilizers may increase drowsiness

Stop use and ask a doctor if

- redness or swelling is present
- symptoms do not get better within 7 days or are accompanied by fever
- fever gets worse or lasts more than 3 days
- cough lasts more than 7 days, comes back, or occurs with fever, rash or headache that lasts

These could be signs of a serious condition.

If pregnant or breast-feeding,

ask a health professional before use.

Overdose warning:

In case of overdose, get medical help or contact a Poison Control Center right away. Quick medical attention is critical for adults as well as for children even if you do not notice any signs or symptoms.

Directions

- take only as recommended - see Overdose warning
- use dose cup or tablespoon (TBSP)
- do not exceed 4 doses per 24 hours

age | dose
adults & children 12 years & over | 30 mL(2TBSP) every 6 hours
children 4 to under 12 years | ask a doctor
children under 4 years | do not use

- If taking Nighttime at night and Daytime during the day, limit total to 4 doses per 24 hours.

Other informaiton

- each 30 mL dose cup contains: sodium 45 mg
- store at room temperature

Tamper Evident: Do not use if imprinted shrink band is missing or broken.

Inactive ingredients

citric acid, D&C yellow#10, FD&C Green# 3, FD&C yellow# 6, flavor, glycerin, polythylene glycol, propylene glycol, purified water, saccharin sodium, sodium benzoate, sodium citrate, sucrose

Questions?

call 1-866-359-3478

Distributed by:

Pharmadel LLC

Seaford, DE 19973

www.sanatos.com